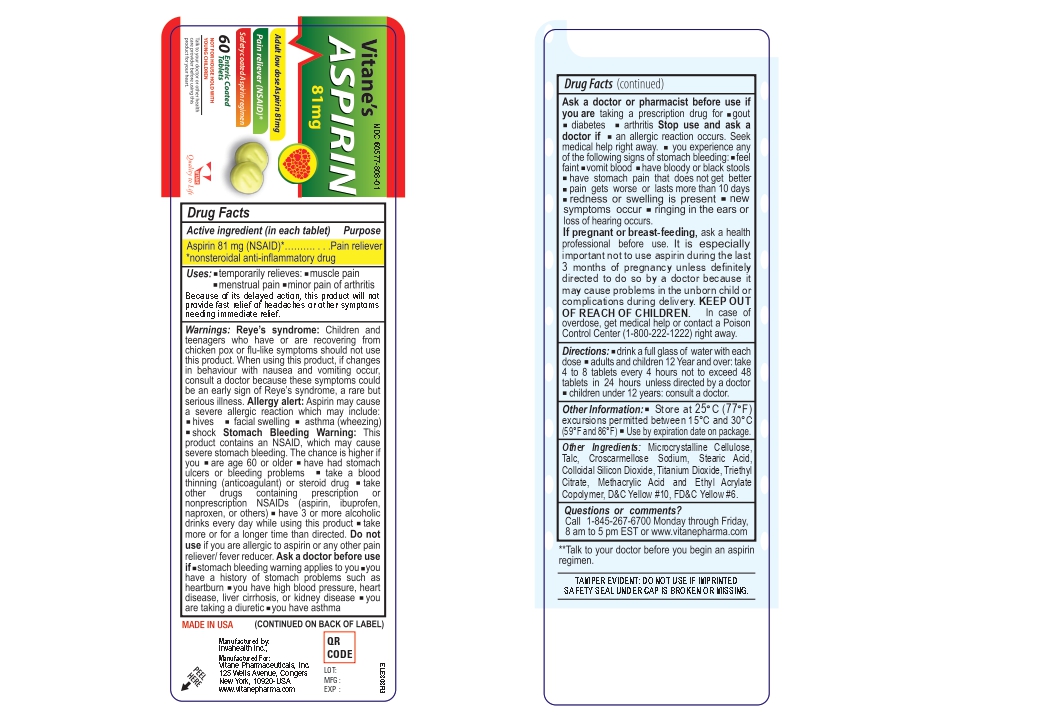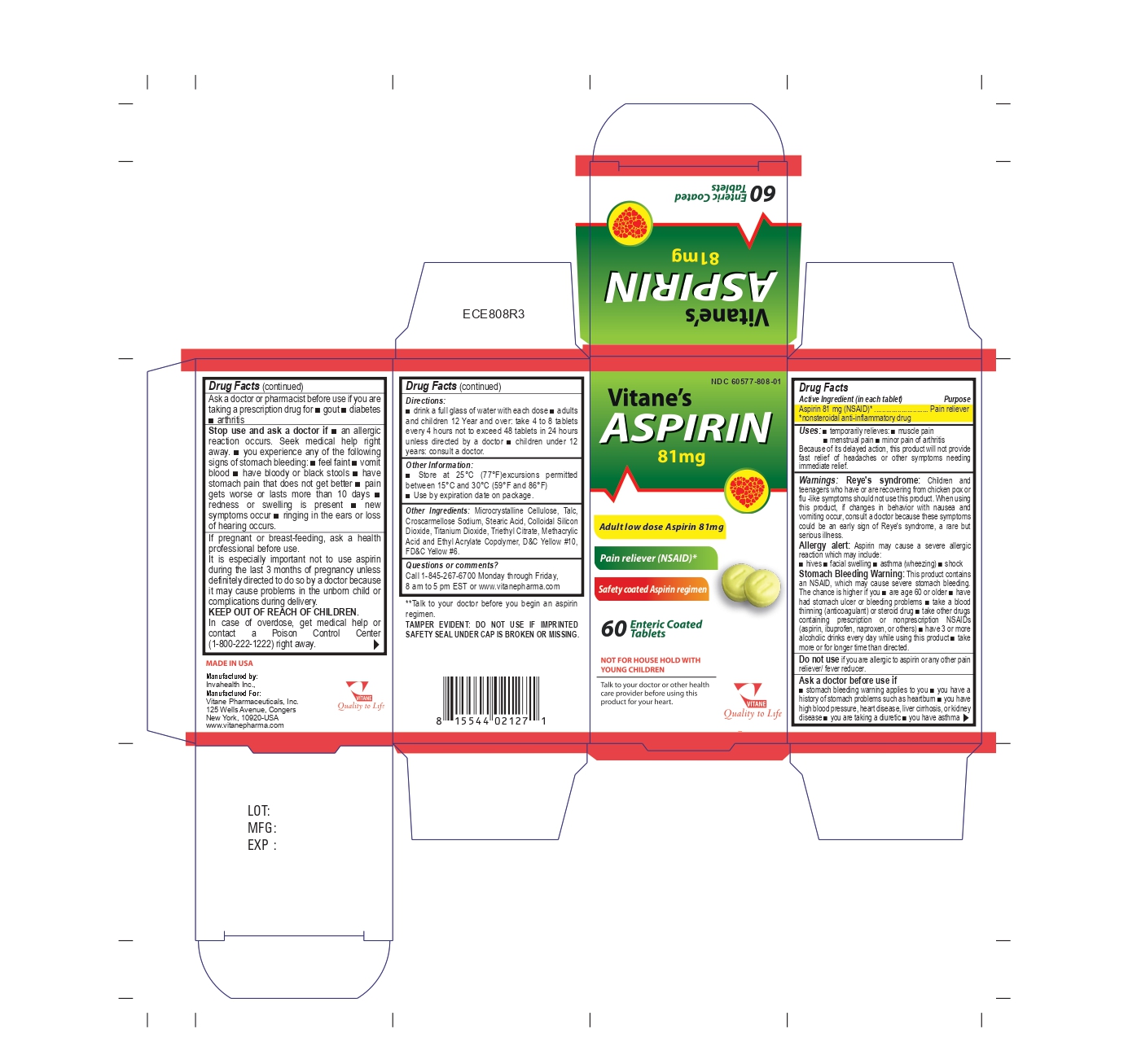 DRUG LABEL: Aspirin 81mg
NDC: 60577-808 | Form: TABLET, DELAYED RELEASE
Manufacturer: VITANE PHARMACEUTICALS, INC
Category: otc | Type: HUMAN OTC DRUG LABEL
Date: 20251015

ACTIVE INGREDIENTS: ASPIRIN 81 mg/1 1
INACTIVE INGREDIENTS: TITANIUM DIOXIDE; CROSCARMELLOSE SODIUM; TRIETHYL CITRATE; METHACRYLIC ACID AND ETHYL ACRYLATE COPOLYMER; D&C YELLOW NO. 10; FD&C YELLOW NO. 6; CELLULOSE, MICROCRYSTALLINE; TALC; STEARIC ACID; SILICON DIOXIDE

ACTIVE INGREDIENT

Aspirin 81 mg (NSAID*)

*nonsteroidal anti-inflamatory drug

PURPOSE

Pain reliever

USES

- Temporarily relieves minor aches and pains
- For use as directed by a doctor for the prevention of recurrent heart attack or stroke

Because of its delayed action, this product will not provide fast relief of headaches or other symptoms needing immediate relief.

WARNINGS

Reye’s Syndrome:

Children and teenagers who have or are recovering from chicken pox or flu-like symptoms should not use this product. When using this product, if changes in behavior with nausea and vomiting occur, consult a doctor because these symptoms could be an early sign of Reye’s syndrome, a rare but serious illness.

ALLERGY ALERT

- Aspirin may cause a severe allergic reaction which may include:
- hives
- facial swelling
- asthma (wheezing)
- shock

Stomach Bleeding Warning:

This product contains an NSAID, which may cause severe stomach bleeding. The chance is higher if you:

- are age 60 or older
- have had stomach ulcers or bleeding problems
- take a blood thinning (anticoagulant) or steroid drug
- take other drugs containing prescription or non-prescription NSAIDs(aspirin, ibuprofen, naproxen, others)
- have 3 or more alcoholic drinks every day while using this product
- take more or for a longer time than directed

DO NOT USE SECTION

Do not use if:

You are allergic to aspirin or any other pain reliever/fever reducer.

ASK A DOCTOR/PHARMACIST

Ask a doctor or pharmacist before use if you are taking a prescription drug for

- gout
- diabetes
- arthritis

STOP USE SECTION

Stop use and ask a doctor if:

- an allergic reaction occurs.
- Seek medical help right away
- you experience any of the following signs of stomach bleeding:
- feel faint
- vomit blood
- have bloody or black stools
- have stomach pain that does not get better
- pain gets worse or lasts more than 10 days
- redness or swelling is present
- new symptoms occur
- ringing in the ears or loss of hearing occurs.

PREGNANCY OR BREAST FEEDING SECTION

If pregnant or breast-feeding, ask a health professional.

It is especially important not to use aspirin during the last 3 months of pregnancy unless definitely directed to do so by a doctor because it may cause problems in the unborn child or complications during delivery.

KEEP OUT OF REACH OF CHILDREN SECTION

Keep out of reach of children. In case of overdose, get medical help or contact a Poison Control Center (1-800-222-1222) right away.

DIRECTIONS

- drink a full glass of water with each dose
- adults and children 12 years and over: take 4 to 8 tablets every 4 hours not to exceed 48 tablets in 24 hours unless directed by a doctor
- children under 12 years: consult a doctor

STORAGE

- Store at 25°C (77°F); excursions permitted between 15°C and 30°C (59°F–86°F)
- Use by expiration date on package.

INACTIVE INGREDIENTS

Microcrystalline Cellulose, Talc, Croscarmellose Sodium, Stearic Acid, Colloidal Silicon Dioxide, Titanium Dioxide, Triethyl Citrate, Methacrylic Acid and Ethyl Acrylate Copolymer, D&C Yellow #10, FD&C Yellow #6

ASK A DOCTOR BEFORE USE

- Stomach bleeding warning applies to you
- You have a history of stomach problems, such as heartburn
- You have a high blood pressure, heart disease, liver cirrhosis, or kidney disease
- You are taking a diuretic
- You have asthma

PRINCIPAL DISPLAY PANEL

NDC 60577-808-01

Vitane's

Aspirin 81mg

Pain Reliever

Aspirin 81 mg (NSAID) Enteric Coated

60 tablets